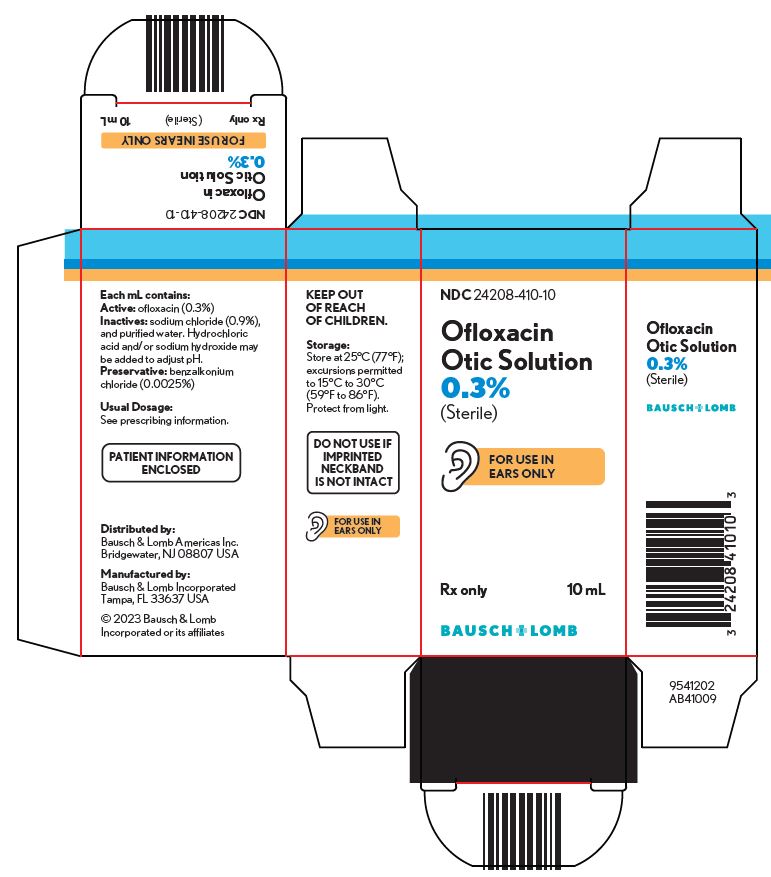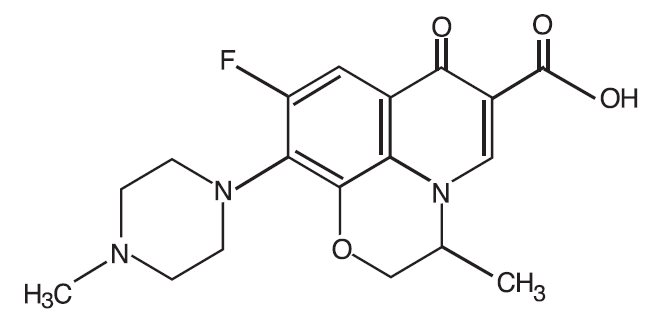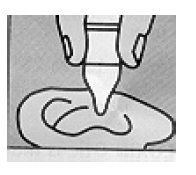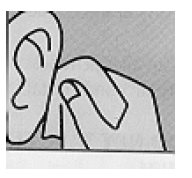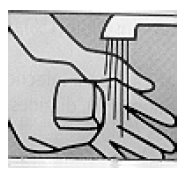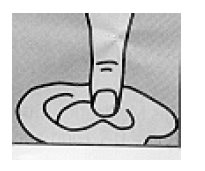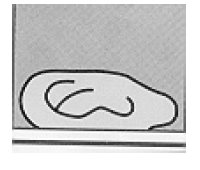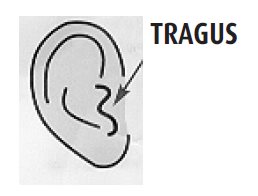 DRUG LABEL: Ofloxacin
NDC: 67296-1925 | Form: SOLUTION
Manufacturer: Redpharm Drug
Category: prescription | Type: HUMAN PRESCRIPTION DRUG LABEL
Date: 20251230

ACTIVE INGREDIENTS: OFLOXACIN 3 mg/1 mL
INACTIVE INGREDIENTS: HYDROCHLORIC ACID; WATER; SODIUM CHLORIDE; SODIUM HYDROXIDE; BENZALKONIUM CHLORIDE 0.2 mg/1 mL

Ofloxacin
Otic Solution
0.3% (Sterile)
Rx only

DESCRIPTION

Ofloxacin otic solution, 0.3% is a sterile aqueous anti-infective (antibacterial) solution for otic use. Chemically, ofloxacin has three condensed 6-membered rings made up of a fluorinated carboxyquinolone with a benzoxazine ring. The chemical name of ofloxacin is: (±)-9-fluoro-2,3-dihydro-3-methyl-10-(4-methyl-1-piperazinyl)-7-oxo- 7H-pyrido [1,2,3- de]-1,4-benzoxazine-6-carboxylic acid. The empirical formula of ofloxacin is C18H20FN3O4and its molecular weight is 361.38. The structural formula is:

Each mL contains: Active: ofloxacin 0.3% (3 mg/mL); Inactives:sodium chloride (0.9%), and purified water. Hydrochloric acid and/or sodium hydroxide may be added to adjust the pH 6.5±0.5. Preservative:benzalkonium chloride (0.0025%).

CLINICAL PHARMACOLOGY

Pharmacokinetics:

Drug concentrations in serum (in subjects with tympanostomy tubes and perforated tympanic membranes), in otorrhea, and in mucosa of the middle ear (in subjects with perforated tympanic membranes) were determined following otic administration of ofloxacin solution. In two single-dose studies, mean ofloxacin serum concentrations were low in adult patients with tympanostomy tubes, with and without otorrhea, after otic administration of a 0.3% solution (4.1 ng/mL (n=3) and 5.4 ng/mL (n=5), respectively). In adults with perforated tympanic membranes, the maximum serum drug level of ofloxacin detected was 10 ng/mL after administration of a 0.3% solution. Ofloxacin was detectable in the middle ear mucosa of some adult subjects with perforated tympanic membranes (11 of 16 subjects). The variability of ofloxacin concentration in middle ear mucosa was high. The concentrations ranged from 1.2 to 602 mcg/g after otic administration of a 0.3% solution. Ofloxacin was present in high concentrations in otorrhea (389 - 2850 mcg/g, n=13) 30 minutes after otic administration of a 0.3% solution in subjects with chronic suppurative otitis media and perforated tympanic membranes. However, the measurement of ofloxacin in the otorrhea does not necessarily reflect the exposure of the middle ear to ofloxacin.

Microbiology:

Ofloxacin has in vitro activity against a wide range of gram-negative and gram-positive microorganisms. Ofloxacin exerts its antibacterial activity by inhibiting DNA gyrase, a bacterial topoisomerase. DNA gyrase is an essential enzyme which controls DNA topology and assists in DNA replication, repair, deactivation, and transcription. Cross-resistance has been observed between ofloxacin and other fluoroquinolones. There is generally no cross-resistance between ofloxacin and other classes of antibacterial agents such as beta-lactams or aminoglycosides.

Ofloxacin has been shown to be active against most isolates of the following microorganisms, both in vitro and clinically in otic infections as described in the INDICATIONS AND USAGEsection.

Aerobes, gram-positive:

Staphylococcus aureus
Streptococcus pneumoniae

Aerobes, gram-negative:

Escherichia coli
Haemophilus influenzae
Moraxella catarrhalis
Proteus mirabilis
Pseudomonas aeruginosa

INDICATIONS AND USAGE

Ofloxacin otic solution, 0.3% is indicated for the treatment of infections caused by susceptible isolates of the designated microorganisms in the specific conditions listed below:

Otitis Externain adults and pediatric patients, 6 months and older, due to Escherichia coli, Pseudomonas aeruginosaand Staphylococcus aureus.
Chronic Suppurative Otitis Mediain patients 12 years and older with perforated tympanic membranes due to Proteus mirabilis, Pseudomonas aeruginosaand Staphylococcus aureus.
Acute Otitis Mediain pediatric patients one year and older with tympanostomy tubes due to Haemophilus influenzae, Moraxella catarrhalis, Pseudomonas aeruginosa, Staphylococcus aureusand Streptococcus pneumoniae.

CONTRAINDICATIONS

Ofloxacin otic solution, 0.3% is contraindicated in patients with a history of hypersensitivity to ofloxacin, to other quinolones, or to any of the components in this medication.

WARNINGS

NOT FOR OPHTHALMIC USE.

NOT FOR INJECTION.
Serious and occasionally fatal hypersensitivity (anaphylactic) reactions, some following the first dose, have been reported in patients receiving systemic quinolones, including ofloxacin. Some reactions were accompanied by cardiovascular collapse, loss of consciousness, angioedema (including laryngeal, pharyngeal or facial edema), airway obstruction, dyspnea, urticaria, and itching. If an allergic reaction to ofloxacin is suspected, stop the drug. Serious acute hypersensitivity reactions may require immediate emergency treatment. Oxygen and airway management, including intubation, should be administered as clinically indicated.

PRECAUTIONS

General:

As with other anti-infective preparations, prolonged use may result in over-growth of nonsusceptible organisms, including fungi. If the infection is not improved after one week, cultures should be obtained to guide further treatment. If otorrhea persists after a full course of therapy, or if two or more episodes of otorrhea occur within six months, further evaluation is recommended to exclude an underlying condition such as cholesteatoma, foreign body, or a tumor.

The systemic administration of quinolones, including ofloxacin at doses much higher than given or absorbed by the otic route, has led to lesions or erosions of the cartilage in weight-bearing joints and other signs of arthropathy in immature animals of various species.

Young growing guinea pigs dosed in the middle ear with 0.3% ofloxacin otic solution showed no systemic effects, lesions or erosions of the cartilage in weight-bearing joints, or other signs of arthropathy. No drug-related structural or functional changes of the cochlea and no lesions in the ossicles were noted in the guinea pig following otic administration of 0.3% ofloxacin for one month.

No signs of local irritation were found when 0.3% ofloxacin was applied topically in the rabbit eye. Ofloxacin was also shown to lack dermal sensitizing potential in the guinea pig maximization study.

Information for Patients:

Avoid contaminating the applicator tip with material from the fingers or other sources. This precaution is necessary if the sterility of the drops is to be preserved. Systemic quinolones, including ofloxacin, have been associated with hypersensitivity reactions, even following a single dose. Discontinue use immediately and contact your physician at the first sign of a rash or allergic reaction.

Otitis Externa:

Prior to administration of ofloxacin otic, the solution should be warmed by holding the bottle in the hand for one or two minutes to avoid dizziness which may result from the instillation of a cold solution. The patient should lie with the affected ear upward, and then the drops should be instilled. This position should be maintained for five minutes to facilitate penetration of the drops into the ear canal. Repeat, if necessary, for the opposite ear (see DOSAGE AND ADMINISTRATION).

Acute Otitis Media and Chronic Suppurative Otitis Media:

Prior to administration of ofloxacin otic, the solution should be warmed by holding the bottle in the hand for one or two minutes to avoid dizziness which may result from the instillation of a cold solution. The patient should lie with the affected ear upward, and then the drops should be instilled. The tragus should then be pumped 4 times by pushing inward to facilitate penetration of the drops into the middle ear. This position should be maintained for five minutes. Repeat, if necessary, for the opposite ear (see DOSAGE AND ADMINISTRATION).

Drug Interactions:

Specific drug interaction studies have not been conducted with ofloxacin otic solution, 0.3%.

Carcinogenesis, Mutagenesis, Impairment of Fertility

Long-term studies to determine the carcinogenic potential of ofloxacin have not been conducted. Ofloxacin was not mutagenic in the Ames test, the sister chromatid exchange assay (Chinese hamster and human cell lines), the unscheduled DNA synthesis (UDS) assay using human fibroblasts, the dominant lethal assay, or the mouse micronucleus assay. Ofloxacin was positive in the rat hepatocyte UDS assay, and in the mouse lymphoma assay. In rats, ofloxacin did not affect male or female reproductive performance at oral doses up to 360 mg/kg/day. This would be over 1000 times the maximum recommended clinical dose, based upon body surface area, assuming total absorption of ofloxacin from the ear of a patient treated with ofloxacin otic solution, 0.3% twice per day.

Pregnancy

Teratogenic effects:

Ofloxacin has been shown to have an embryocidal effect in rats at a dose of 810 mg/kg/day and in rabbits at 160 mg/kg/day.

These dosages resulted in decreased fetal body weights and increased fetal mortality in rats and rabbits, respectively. Minor fetal skeletal variations were reported in rats receiving doses of 810 mg/kg/day. Ofloxacin has not been shown to be teratogenic at doses as high as 810 mg/kg/day and 160 mg/kg/day when administered to pregnant rats and rabbits, respectively.

Ofloxacin has not been shown to have any adverse effects on the developing embryo or fetus at doses relevant to the amount of ofloxacin that will be delivered ototopically at the recommended clinical doses.

Nonteratogenic Effects:

Additional studies in the rat demonstrated that doses up to 360 mg/kg/day during late gestation had no adverse effects on late fetal development, labor, delivery, lactation, neonatal viability, or growth of the newborn. There are, however, no adequate and well-controlled studies in pregnant women. Ofloxacin otic solution, 0.3% should be used during pregnancy only if the potential benefit justifies the potential risk to the fetus.

Nursing Mothers:

In nursing women, a single 200 mg oral dose resulted in concentrations of ofloxacin in milk which were similar to those found in plasma. It is not known whether ofloxacin is excreted in human milk following topical otic administration. Because of the potential for serious adverse reactions from ofloxacin in nursing infants, a decision should be made whether to discontinue nursing or to discontinue the drug, taking into account the importance of the drug to the mother.

Pediatric Use:

Safety and efficacy have been demonstrated in pediatric patients of the following ages for the listed indications:

■ six months and older: otitis externa with intact tympanic membranes
■ one year and older: acute otitis media with tympanostomy tubes
■ twelve years and older: chronic suppurative otitis media with perforated tympanic membranes

Safety and efficacy in pediatric patients below these ages have not been established.

Although no data are available on patients less than age 6 months, there are no known safety concerns or differences in the disease process in this population that will preclude use of this product.

No changes in hearing function occurred in 30 pediatric subjects treated with ofloxacin otic and tested for audiometric parameters. Although quinolones, including ofloxacin, have been shown to cause arthropathy in immature animals after systemic administration, young growing guinea pigs dosed in the middle ear with 0.3% ofloxacin otic solution for one month showed no systemic effects, quinolone-induced lesions, erosions of the cartilage in weight-bearing joints, or other signs of arthropathy.

ADVERSE REACTIONS

Subjects with Otitis Externa
In the phase III clinical trials performed in support of once-daily dosing, 799 subjects with otitis externa and intact tympanic membranes were treated with ofloxacin otic solution. The studies, which served as the basis for approval, were 020 (pediatric, adolescents and adults), 016 (adolescents and adults) and 017 (pediatric). The following treatment-related adverse events occurred in two or more of the subjects:

Incidence Rate
Adverse Event | Studies 002/003* BID (N=229) | Studies 016/017* QD (N=310) | Study 020* QD (N=489)
Application Site Reaction | 3% | 16.8% | 0.6%
Pruritus | 4% | 1.2% | 1.0%
Earache | 1% | 0.6% | 0.8%
Dizziness | 1% | 0.0% | 0.6%
Headache | 0% | 0.3% | 0.2%
Vertigo | 1% | 0.0% | 0.0%

* Studies 002/003 (BID) and 016/017 (QD) were active-controlled and comparative. Study 020 (QD) was open and non-comparative.

An unexpected increased incidence of application site reaction was seen in studies 016/017 and was similar for both ofloxacin and the active control drug (neomycin-polymyxin B sulfate-hydrocortisone). This finding is believed to be the result of specific questioning of the subjects regarding the incidence of application site reactions.

In once daily dosing studies, there were also single reports of nausea, seborrhea, transient loss of hearing, tinnitus, otitis externa, otitis media, tremor, hypertension and fungal infection.

In twice daily dosing studies, the following treatment-related adverse events were each reported in a single subject: dermatitis, eczema, erythematous rash, follicular rash, hypoaesthesia, tinnitus, dyspepsia, hot flushes, flushing and otorrhagia.

Subjects with Acute Otitis Media with Tympanostomy Tubes (AOM TT) and Subjects with Chronic Suppurative Otitis Media (CSOM) with Perforated Tympanic Membranes:

In phase III clinical trials which formed the basis for approval, the following treatment-related adverse events occurred in 1% or more of the 656 subjects with non-intact tympanic membranes in AOM TT or CSOM treated twice daily with ofloxacin otic solution:

Adverse Event | Incidence (N=656)
Taste Perversion; Earache; Pruritus; Paraesthesia; Rash; Dizziness | 7%; 1%; 1%; 1%; 1%; 1%

Other treatment-related adverse reactions reported in subjects with non-intact tympanic membranes included: diarrhea (0.6%), nausea (0.3%), vomiting (0.3%), dry mouth (0.5%), headache (0.3%), vertigo (0.5%), otorrhagia (0.6%), tinnitus (0.3%), and fever (0.3%). The following treatment-related adverse events were each reported in a single subject: application site reaction, otitis externa, urticaria, abdominal pain, dysaesthesia, hyperkinesia, halitosis, inflammation, pain, insomnia, coughing, pharyngitis, rhinitis, sinusitis, and tachycardia.

Post-Marketing Adverse Events

Cases of uncommon transient neuropsychiatric disturbances have been included in spontaneous post-marketing reports. A causal relationship with ofloxacin otic solution, 0.3% is unknown.

To report SUSPECTED ADVERSE REACTIONS, contact Bausch & Lomb Incorporated at 1-800-553-5340 or FDA at 1-800-FDA-1088 or www.fda.gov/medwatch.

DOSAGE AND ADMINISTRATION

Otitis Externa:The recommended dosage regimen for the treatment of otitis externa is:

For pediatric patients (from 6 months to 13 years old): Five drops (0.25 mL, 0.75 mg ofloxacin) instilled into the affected ear once daily for seven days.

For patients 13 years and older: Ten drops (0.5 mL, 1.5 mg ofloxacin) instilled into the affected ear once daily for seven days.

The solution should be warmed by holding the bottle in the hand for one or two minutes to avoid dizziness which may result from the instillation of a cold solution. The patient should lie with the affected ear upward, and then the drops should be instilled. This position should be maintained for five minutes to facilitate penetration of the drops into the ear canal. Repeat, if necessary, for the opposite ear.

Acute Otitis Media in pediatric patients with tympanostomy tubes:The recommended dosage regimen for the treatment of acute otitis media in pediatric patients (from 1 to 12 years old) with tympanostomy tubes is:

1. Five drops (0.25 mL, 0.75 mg ofloxacin) instilled into the affected ear twice daily for ten days. The solution should be warmed by holding the bottle in the hand for one or two minutes to avoid dizziness which may result from the instillation of a cold solution.
2. The patient should lie with the affected ear upward, and then the drops should be instilled. The tragus should then be pumped 4 times by pushing inward to facilitate penetration of the drops into the middle ear. This position should be maintained for five minutes. Repeat, if necessary, for the opposite ear.

Chronic Suppurative Otitis Media with perforated tympanic membranes:The recommended dosage regimen for the treatment of chronic suppurative otitis media with perforated tympanic membranes in patients 12 years and older is:

1. Ten drops (0.5 mL, 1.5 mg ofloxacin) instilled into the affected ear twice daily for fourteen days. The solution should be warmed by holding the bottle in the hand for one or two minutes to avoid dizziness which may result from the instillation of a cold solution. The patient should lie with the affected ear upward, before instilling the drops. The tragus should then be pumped 4 times by pushing inward to facilitate penetration into the middle ear. This position should be maintained for five minutes. Repeat, if necessary, for the opposite ear.

HOW SUPPLIED

Ofloxacin otic solution, 0.3% is supplied in plastic dropper bottles in the following sizes:

NDC 24208-410-05 5 mL
NDC 24208-410-10 10 mL

Storage:

Store at 25ºC (77ºF); excursions permitted to 15ºC to 30ºC (59ºF to 86ºF). Protect from light.

Distributed by:
Bausch & Lomb Americas Inc.
Bridgewater, NJ 08807 USA

Manufactured by:
Bausch & Lomb Incorporated
Tampa, FL 33637 USA
© 2023 Bausch & Lomb Incorporated or its affiliates

Revised 05/2023

9047606 (Folded)
9047706 (Flat)

DO NOT USE IF IMPRINTED NECKBAND IS NOT INTACT

Ofloxacin
(Oh floxʹ a sin)
Otic Solution
0.3% (Sterile)

Patient Information

IMPORTANT PATIENT INFORMATION AND INSTRUCTIONS. READ BEFORE USE.

What is ofloxacin otic solution, 0.3%?

Ofloxacin otic solution, 0.3% is an antibiotic in a sterile solution used to treat ear infections caused by certain bacteria found in:

■ patients (12 years and older) who have a middle ear infection and have a hole in the eardrum
■ pediatric patients (between 1 and 12 years of age) who have a middle ear infection and have a tube in the eardrum
■ patients (6 months and older) who have an infection in the ear canal.

Middle Ear Infection:A middle ear infection is a bacterial infection behind the eardrum. People with a hole or a tube in the eardrum may notice a discharge (fluid draining) from the ear canal.

Ear Canal Infection:An ear canal infection (also known as “Swimmer’s Ear”) is a bacterial infection of the ear canal. The ear canal and the outer part of the ear may swell, turn red, and be painful. Also, a fluid discharge may appear in the ear canal.

Who should NOT use ofloxacin otic solution, 0.3%?

■ Do not use this product if you are allergic to ofloxacin or to other quinolone antibiotics.
■ Do not give this product to pediatric patients who:

- ■ have an ear canal infection and are less than 6 months of age because no data were collected from this population
- ■ have a middle ear infection and have a tube in the eardrum and are less than one year of age because no data were collected from this population
- ■ have a middle ear infection and have a hole in the eardrum and are less than twelve years of age because no data were collected from this population

How should ofloxacin otic solution, 0.3% be given?

1. Wash hands

The person giving ofloxacin otic solution, 0.3% should wash his/her hands with soap and water.

2. Clean ear and warm bottle

Gently clean any discharge that can be removed easily from the outer ear.

DO NOT INSERT ANY OBJECT OR SWAB INTO THE EAR CANAL.

Hold the bottle of ofloxacin otic solution, 0.3% in the hand for one or two minutes to warm the solution.

3. Add drops

For a Middle Ear Infection: The person receiving ofloxacin otic solution, 0.3% should lie on his/her side with the infected ear up. Patients (12 and older) should have 10 dropsof ofloxacin otic solution, 0.3% put into the infected ear. Pediatric patients under 12 should have 5 dropsput into the infected ear. The tip of the bottle should not touch the fingers or the ear or any other surfaces.

For an Ear Canal Infection (“Swimmer’s Ear”):

The person receiving ofloxacin otic should lie on his/her side with the infected ear up. Patients (13 and older) should have 10 drops of ofloxacin otic put into the infected ear. Pediatric patients under 13 should have 5 drops put into the infected ear. The tip of the bottle should not touch the fingers or the ear or any other surfaces.

BE SURE TO FOLLOW THE INSTRUCTIONS BELOW FOR THE PATIENT'S SPECIFIC EAR INFECTION.

4. Press ear or pull ear

For a Middle Ear Infection:While the person receiving ofloxacin otic solution, 0.3% lies on his/her side, the person giving the drops should gently press the TRAGUS(see diagram) 4 times in a pumping motion. This will allow the drops to pass through the hole or tube in the eardrum and into the middle ear.

For an Ear Canal Infection (“Swimmer’s Ear”):

While the person receiving the drops lies on his/her side, the person giving the drops should gently pull the outer ear upward and backward. This will allow the ear drops to flow down into the ear canal.

5. Stay on side

The person who received the ear drops should remain on his/her side for at least 5 minutes.

Repeat Steps 2-5 for the other ear if both ears are infected.

How often should ofloxacin otic solution, 0.3% be given?

In patients with an Ear Canal Infection (“Swimmer’s Ear”), ofloxacin otic ear drops should be given once daily at about the same time each day (for example, 8 AM or 8 PM) in each infected ear unless the doctor has instructed otherwise.

In patients with a middle ear infection, ofloxacin otic solution, 0.3% ear drops should be given 2 times each day (about 12 hours apart, for example, 8 AM and 8 PM) in each infected ear unless the doctor has instructed otherwise. The best times to use the ear drops are in the morning and at night. It is very important to use the ear drops for as long as the doctor has instructed, even if the symptoms improve. If ofloxacin otic solution, 0.3% ear drops are not used for as long as the doctor has instructed, the infection may be more likely to return.

What if a dose is missed?

In patients with an Ear Canal Infection (“Swimmer's Ear”), it is important that you take the drops every day. If you miss a dose which may have been scheduled for earlier in the day, (for example, 8 AM), you should take that day’s dose as soon as possible and then go back to your regular daily dosing schedule.
In patients with a Middle Ear Infection, if a dose of ofloxacin otic solution, 0.3% is missed, it should be given as soon as possible. However, if it is almost time for the next dose, skip the missed dose and go back to the regular dosing schedule. Do not use a double dose unless the doctor has instructed you to do so. If the infection is not improved after one week, you should consult your doctor. If you have two or more episodes of drainage within six months, it is recommended you see your doctor for further evaluation.

What activities should be avoided while using ofloxacin otic solution, 0.3%?

It is important that the infected ear(s) remain clean and dry. When bathing, avoid getting the infected ear(s) wet. Avoid swimming unless the doctor has instructed otherwise.

What are some of the possible side effects of ofloxacin otic solution, 0.3%?

During the testing of ofloxacin otic in external ear infections, the most common side effect was discomfort upon application which happened in 7% of patients. If the pain is severe, the medication should be stopped and you should contact your doctor. Other side effects were: itching (1%), earache (0.8%), and dizziness (0.4%).

During the testing of ofloxacin otic solution, 0.3% in middle ear infections, the most common side effect was a bitter taste which happened in 7% of patients with a middle ear infection. This may occur when some of the drops pass from the middle ear to the back of the mouth. This side effect is not serious and there is no need to stop the medicine if this should happen. Other side effects which were found in 1% of the patients were: earache, itching, abnormal sensation, rash, and dizziness.

Call your doctor about these or other side effects if they occur.

If a rash or an allergic reaction to ofloxacin otic solution, 0.3% occurs, stop using the product and contact your doctor.

DO NOT TAKE ofloxacin otic solution, 0.3% BY MOUTH.

If ofloxacin otic solution, 0.3% is accidentally swallowed or overdose occurs, call the doctor immediately. This medicine is available only with a doctor’s prescription. Use only as directed. Do not use this medicine if outdated.

If you wish to learn more about ofloxacin otic solution, 0.3% ask the doctor or pharmacist. See complete

Prescribing Information.

Storage:Store at 77ºF (25ºC); excursions permitted to 59ºF to 86ºF (15ºC to 30ºC). Protect from light.

Distributed by:
Bausch & Lomb Americas Inc.
Bridgewater, NJ 08807 USA
Manufactured by:
Bausch & Lomb Incorporated
Tampa, FL 33637 USA
© 2023 Bausch & Lomb Incorporated or its affiliates

This Patient Information has been approved by the U.S. Food and Drug Administration.

Revised 05/2023
9047606 (Folded)
9047706 (Flat)

Principal Display Panel – Ofloxacin Otic Solution 0.3% (Sterile) - 10 mL Carton

NDC24208-410-10

Ofloxacin
Otic Solution
0.3%

(Sterile)

(ear icon) FOR USE IN EARS ONLY

Rx only

10 mL

BAUSCH + LOMB

9541202
AB41009